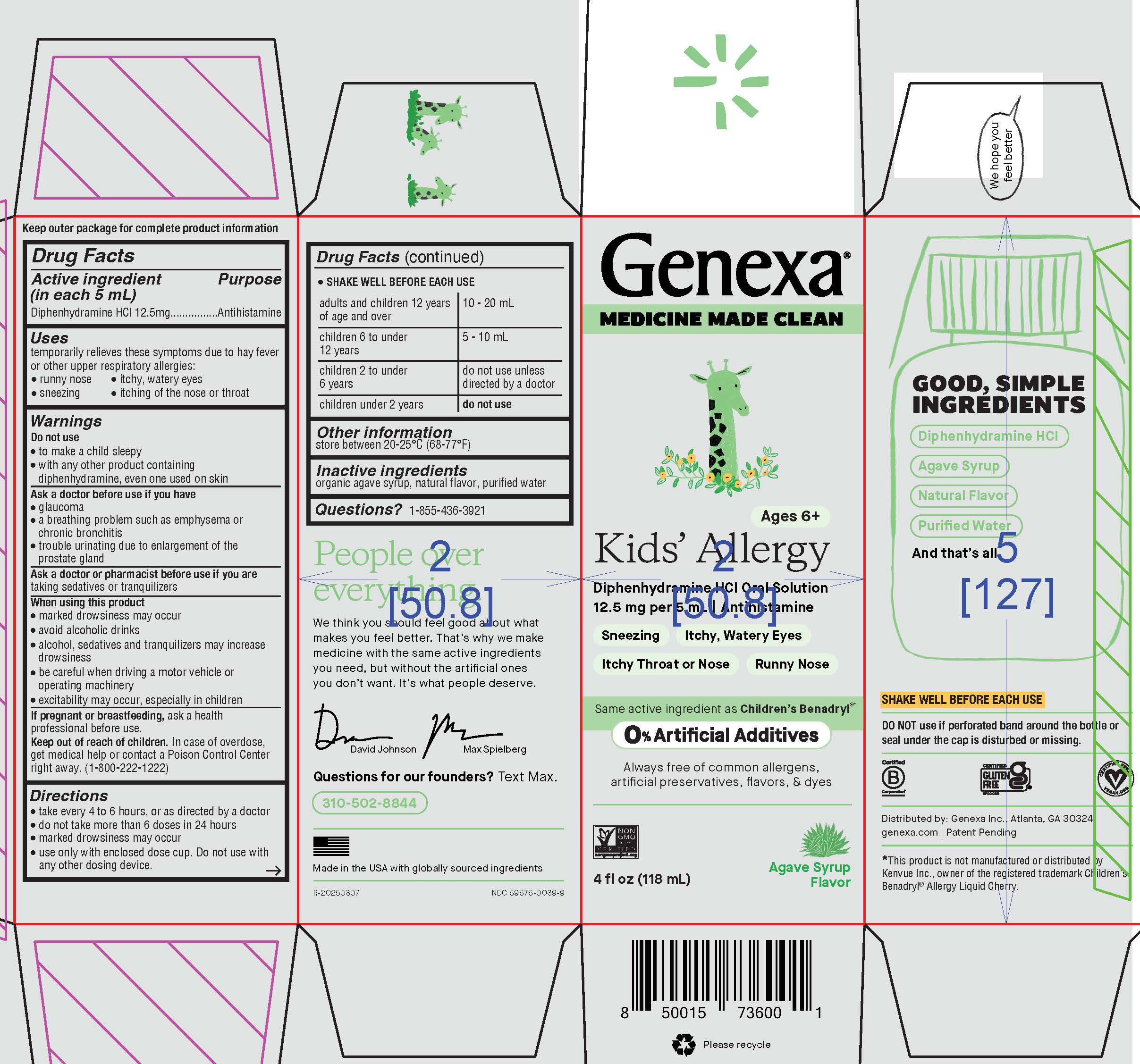 DRUG LABEL: Kids Allergy
NDC: 69676-0039 | Form: LIQUID
Manufacturer: Genexa Inc.
Category: otc | Type: HUMAN OTC DRUG LABEL
Date: 20260225

ACTIVE INGREDIENTS: DIPHENHYDRAMINE HYDROCHLORIDE 12.5 mg/5 mL
INACTIVE INGREDIENTS: AGAVE TEQUILANA JUICE; WATER

Kids' Allergy Liquid

Drug Facts

Active ingredient (in each 5 mL)

Diphenhydramine HCl 12.5 mg

Purpose

Antihistamine

Uses

temporarily relieves these symptoms due to hay fever or other upper respiratory allergies:

- runny nose
- sneezing
- itchy, watery eyes
- itching of the nose or throat

Warnings

Do not use

- to make a child sleepy
- with any other product containing diphenhydramine, even one used on skin

Ask a doctor before use if you have

- glaucoma
- a breathing problem such as emphysema or chronic bronchitis
- trouble urinating due to enlargement of the prostate gland

Ask a doctor or pharmacist before use if you are taking sedatives or tranquilizers

When using this product

- marked drowsiness may occur
- avoid alcoholic drinks
- alcohol, sedatives and tranquilizers may increase drowsiness
- be careful when driving a motor vehicle or operating machinery
- excitability may occur, especially in children

PREGNANCY OR BREAST FEEDING

If pregnant or breastfeeding, ask a health professional before use.

Keep out of reach of children. In case of overdose, get medical help or contact a Poison Control Center right away. (1-800-222-1222)

Directions

- take every 4 to 6 hours, or as directed by a doctor
- do not take more than 6 doses in 24 hours
- marked drowsiness may occur
- use only with enclosed dose cup. Do not use with any other dosing device.
- SHAKE WELL BEFORE EACH USE

adults and children 12 years of age and over | 10 - 20 mL
children 6 to under 12 years | 5 - 10 mL
children 2 to under 6 years | do not use unless directed by a doctor
children under 2 years | do not use

Other information

store between 20-25°C (68-77°F)

Inactive ingredients

organic agave syrup, natural flavor, purified water

Questions?

1-855-436-3921

Made in the USA with globally sourced ingredients.

NDC 69676-0039-9

SHAKE WELL BEFORE EACH USE

DO NOT use if perforated band around the bottle or seal under the cap is disturbed or missing.

Distributed by: Genexa Inc., Atlanta, GA 30324

genexa.com | Patent Pending

*This product is not manufactured or distributed by Kenvue Inc., owner of the registered trademark Children's Benadryl® Allergy Liquid Cherry.

Directions

- take every 4 to 6 hours, or as directed by a doctor
- do not take more than 6 doses in 24 hours
- marked drowsiness may occur
- use only with enclosed dose cup. Do not use with any other dosing device.
- SHAKE WELL BEFORE EACH USE

adults and children 12 years of age and over | 10 - 20 mL
children 6 to under 12 years | 5 - 10 mL
children 2 to under 6 years | do not use unless directed by a doctor
children under 2 years | do not use

PACKAGE LABEL

Genexa®

MEDICINE MADE CLEAN

Ages 6+

Kids' Allergy

Diphenhydramine HCl Oral Solution

12.5 mg per 5 mL | Antihistamine

Sneezing

Itchy, Watery Eyes

Itchy Throat or Nose

Runny Nose

Same active ingredient as Children's Benadryl®*

0% artificial additives

Always free of common allergens, artificial preservatives, flavors, & dyes

Agave Syrup Flavor

4 FL OZ (118 mL)